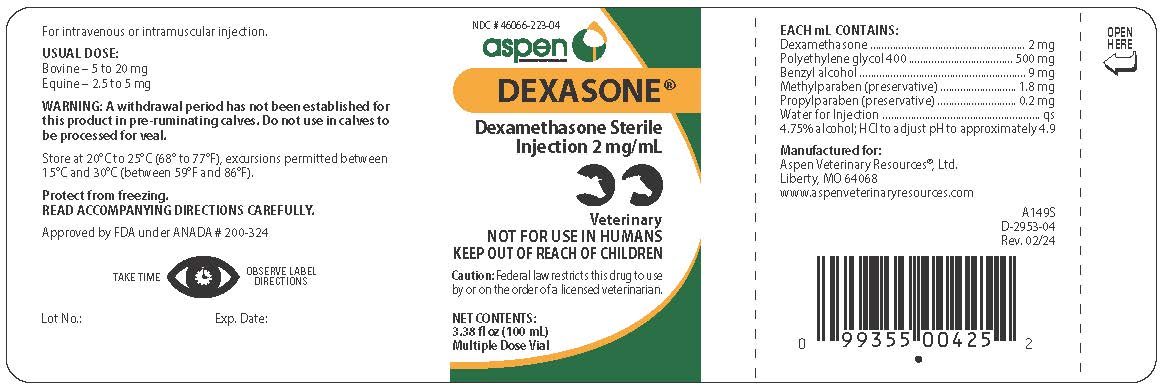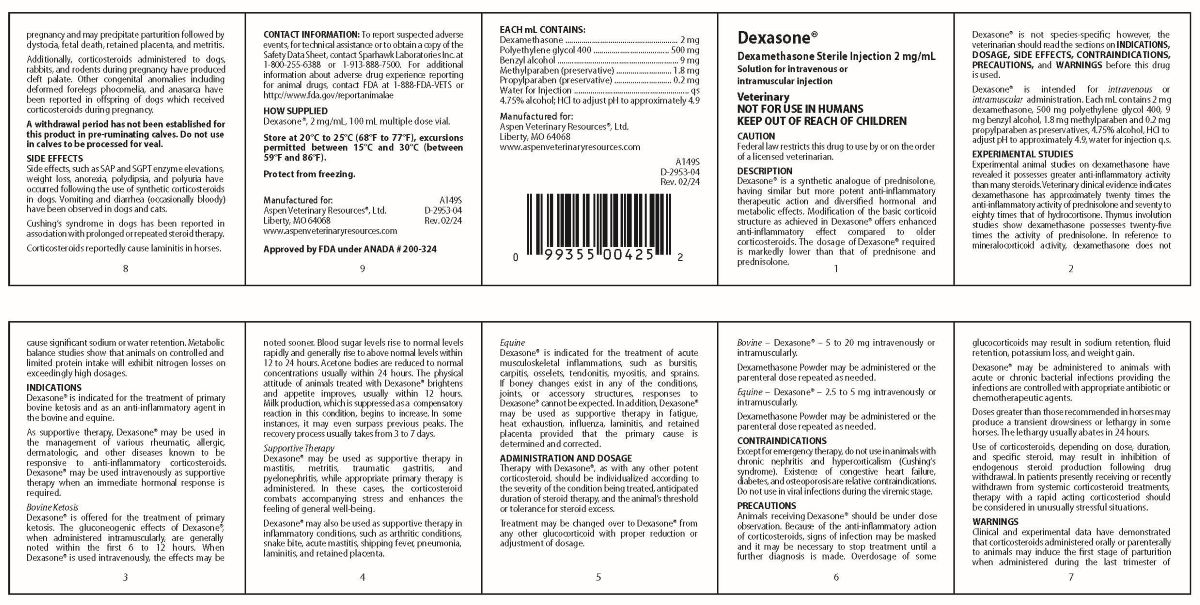 DRUG LABEL: DEXASONE
NDC: 46066-223 | Form: INJECTION, SOLUTION
Manufacturer: Aspen Veterinary Resources, Ltd.
Category: animal | Type: PRESCRIPTION ANIMAL DRUG LABEL
Date: 20251021

ACTIVE INGREDIENTS: DEXAMETHASONE 2 mg/1 mL
INACTIVE INGREDIENTS: BENZYL ALCOHOL; POLYETHYLENE GLYCOL 400; ALCOHOL; METHYLPARABEN; PROPYLPARABEN; WATER; HYDROCHLORIC ACID

Dexasone® Dexamethasone Sterile Injection 2 mg/mL

DESCRIPTION

Dexasone®

Dexamethasone Sterile Injection 2 mg/mL

Veterinary

NOT FOR USE IN HUMANS
KEEP OUT OF REACH OF CHILDREN

CAUTION: Federal Law restricts this drug to use by or on the order of a licensed veterinarian.

DESCRIPTION
Dexasone® is a synthetic analogue of prednisolone, having similar but more potent anti-inflammatory therapeutic action and diversified hormonal and metabolic effects. Modification of the basic corticoid structure as achieved in Dexasone® offers enhanced anti-inflammatory effect compared to older corticosteroids. The dosage of Dexasone® required is markedly lower than that of prednisone and prednisolone.

Dexasone® is not species-specific; however, the veterinarian should read the sections on INDICATIONS, DOSAGE, SIDE EFFECTS, CONTRAINDICATIONS, PRECAUTIONS, and WARNINGS before this drug is used.

Dexasone® is intended for intravenous or intramuscular administration. Each mL contains 2 mg dexamethasone, 500 mg polyethylene glycol 400, 9 mg benzyl alcohol, 1.8 mg methylparaben and 0.2 mg propylparaben as preservatives, 4.75% alcohol, HCl to adjust pH to approximately 4.9, water for injection q.s.

EXPERIMENTAL STUDIES

Experimental animal studies on dexamethasone have revealed it possesses greater anti-inflammatory activity than many steroids. Veterinary clinical evidence indicates dexamethasone has approximately twenty times the anti-inflammatory activity of prednisolone and seventy to eighty times that of hydrocortisone. Thymus involution studies show dexamethasone possesses twenty-five times the activity of prednisolone. In reference to mineralocorticoid activity, dexamethasone does not cause significant sodium or water retention. Metabolic balance studies show that animals on controlled and limited protein intake will exhibit nitrogen losses on exceedingly high dosages.

INDICATIONS

Dexasone® is indicated for the treatment of primary bovine ketosis and as an anti-inflammatory agent in the bovine and equine.

As supportive therapy, Dexasone® may be used in the management of various rheumatic, allergic, dermatologic, and other diseases known to be responsive to anti-inflammatory corticosteroids. Dexasone® may be used intravenously as supportive therapy when an immediate hormonal response is required.

Bovine Ketosis Dexasone® is offered for the treatment of primary ketosis. The gluconeogenic effects of Dexasone®, when administered intramuscularly, are generally noted within the first 6 to 12 hours. When Dexasone® is used intravenously, the effects may be noted sooner. Blood sugar levels rise to normal levels rapidly and generally rise to above normal levels within 12 to 24 hours. Acetone bodies are reduced to normal concentrations usually within 24 hours. The physical attitude of animals treated with Dexasone® brightens and appetite improves, usually within 12 hours. Milk production, which is suppressed as a compensatory reaction in this condition, begins to increase. In some instances, it may even surpass previous peaks. The recovery process usually takes from 3 to 7 days.

Supportive Therapy Dexasone® may be used as supportive therapy in mastitis, metritis, traumatic gastritis, and pyelonephritis, while appropriate primary therapy is administered. In these cases, the corticosteroid combats accompanying stress and enhances the feeling of general well-being. Dexasone® may also be used as supportive therapy in inflammatory conditions, such as arthritic conditions, snake bite, acute mastitis, shipping fever, pneumonia, laminitis, and retained placenta.

Equine Dexasone® is indicated for the treatment of acute musculoskeletal inflammations, such as bursitis, carpitis, osselets, tendonitis, myositis, and sprains. If boney changes exist in any of the conditions, joints, or accessory structures, responses to Dexasone® cannot be expected. In addition, Dexasone® may be used as supportive therapy in fatigue, heat exhaustion, influenza, laminitis, and retained placenta provided that the primary cause is determined and corrected.

ADMINISTRATION AND DOSAGE

Therapy with Dexasone®, as with any other potent corticosteroid, should be individualized according to the severity of the condition being treated, anticipated duration of steroid therapy, and the animal's threshold or tolerance for steroid excess.

Treatment may be changed over to Dexasone® from any other glucocorticoid with proper reduction or adjustment of dosage.

Bovine - Dexasone® - 5 to 20 mg intravenously or intramuscularly.

Dexamethasone Powder may be administered or the parenteral dose repeated as needed.

Equine - Dexasone® - 2.5 to 5 mg intravenously or intramuscularly.

Dexamethasone Powder may be administered or the parenteral dose repeated as needed.

CONTRAINDICATIONS

Except for emergency therapy, do not use in animals with chronic nephritis and hypercorticalism (Cushing's syndrome). Existence of congestive heart failure, diabetes, and osteoporosis are relative contraindications. Do not use in viral infections during the viremic stage.

PRECAUTIONS

Animals receiving Dexasone® should be under close observation. Because of the anti-inflammatory action of corticosteroids, signs of infection may be masked and it may be necessary to stop treatment until a further diagnosis is made. Overdosage of some glucocorticoids may result in sodium retention, fluid retention, potassium loss, and weight gain.

Dexasone® may be administered to animals with acute or chronic bacterial infections providing the infections are controlled with appropriate antibiotic or chemotherapeutic agents.

Doses greater than those recommended in horses may produce a transient drowsiness or lethargy in some horses. The lethargy usually abates in 24 hours.

Use of corticosteroids, depending on dose, duration, and specific steroid, may result in inhibition of endogenous steroid production following drug withdrawal. In patients presently receiving or recently withdrawn from systemic corticosteroid treatments, therapy with a rapid acting corticosteroid should be considered in unusually stressful situations.

WARNINGS

Clinical and experimental data have demonstrated that corticosteroids administered orally or parenterally to animals may induce the first stage of parturition when administered during the last trimester of pregnancy and may precipitate parturition followed by dystocia, fetal death, retained placenta, and metritis.

Additionally, corticosteroids administered to dogs, rabbits, and rodents during pregnancy have produced cleft palate. Other congenital anomalies including deformed forelegs phocomelia, and anasarca have been reported in offspring of dogs which received corticosteroids during pregnancy.

A withdrawal period has not been established for this product in pre-ruminating calves. Do not use in calves to be processed for veal.

SIDE EFFECTS

Side effects, such as SAP and SGPT enzyme elevations, weight loss, anorexia, polydipsia, and polyuria have occurred following the use of synthetic corticosteroids in dogs. Vomiting and diarrhea (occasionally bloody) have been observed in dogs and cats.

Cushing's syndrome in dogs has been reported in association with prolonged or repeated steroid therapy.

Corticosteroids reportedly cause laminitis in horses.

CONTACT INFORMATION

To report suspected adverse
events, for technical assistance or to obtain a copy of the
Safety Data Sheet, contact Sparhawk Laboratories Inc. at
1-800-255-6388 or 1-913-888-7500. For additional
information about adverse drug experience reporting
for animal drugs, contact FDA at 1-888-FDA-VETS or
http://www.fda.gov/reportanimalae

HOW SUPPLIED

Dexasone®, 2 mg/mL, 100 mL multiple dose vial.

Store at controlled room temperature of 20°C to 25°C (68° to 77°F), excursions permitted between 15°C and 30°C (between 59°F and 86°F).

Protect from freezing.

Manufactured for:
Aspen Veterinary Resources®, Ltd.
Liberty, MO 64068
www.aspenveterinaryresources.com

Approved by FDA under ANADA # 200-324

COMPONENTS

Each mL contains:
Dexamethasone..........................2 mg
Polyethylene glycol 400...........500 mg
Benzyl alcohol............................9 mg
Methylparaben (preservative).....1.8 mg
Propylparaben (preservative)......0.2 mg
Water for Injection...........................qs
4.75% alcohol; HCl to adjust pH to approximately 4.9

Usual Dose

For intravenous or intramuscular injection

Bovine-5 to 20 mg
Equine-2.5 to 5 mg

WARNING

A withdrawal period has not been established for this product in pre-ruminating calves. Do not use in calves to be processed for veal.

Store at 20°C to 25°C (68° to 77°F), excursions permitted between 15°C and 30°C (between 59°F and 86°F).

Protect from freezing.

READ ACCOMPANYING DIRECTIONS CAREFULLY.

Approved by FDA under ANADA # 200-324